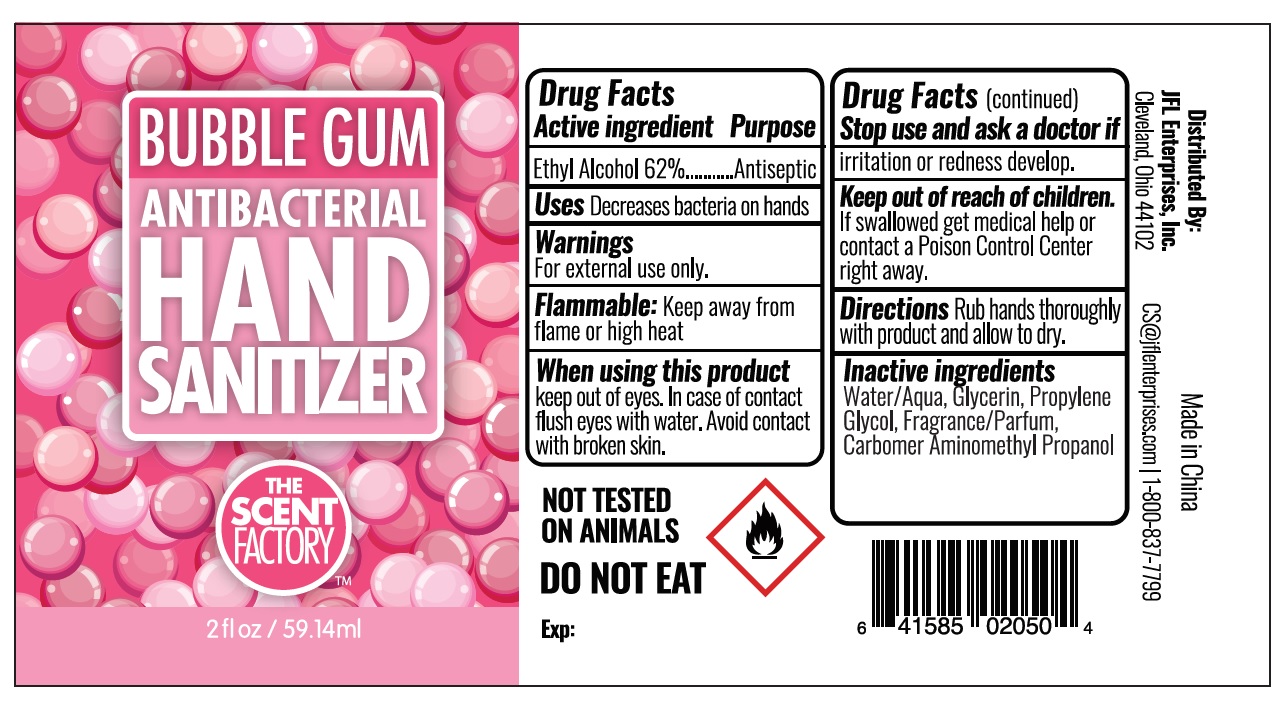 DRUG LABEL: Hand Sanitizer
NDC: 71246-0004 | Form: GEL
Manufacturer: JFL Enterprises, Inc.
Category: otc | Type: HUMAN OTC DRUG LABEL
Date: 20200613

ACTIVE INGREDIENTS: ALCOHOL 620 mL/1000 mL
INACTIVE INGREDIENTS: WATER; GLYCERIN; PROPYLENE GLYCOL; AMINOMETHYLPROPANOL; CARBOMER HOMOPOLYMER, UNSPECIFIED TYPE

Bubble Gum - Antibacterial Hand Sanitizer

Active Ingredient - Ethyl Alcohol 62%.....Antiseptic

Purpose - Antiseptic

Use

To decrease bacteria on hands

Warnings

For external use only

Flammable, keep away from fire or flame

Keep out of reach of children

If accidently swallowed, get medical help or contact a Poison Control Center right away

WHEN USING SECTION

Keep out of eyes,In case of contact flush eyes with water.

Avoid contact with broken skin.

ASK DOCTOR

Discontinue use if irritation or redness develop.

Directions

- Rub hands thoroughly with product and allow to dry.

Inactive Ingredients

Water, Glycerin, Carbomer, Fragrance, Propylene Glycol, Carbomer Aminomethyl Propanol